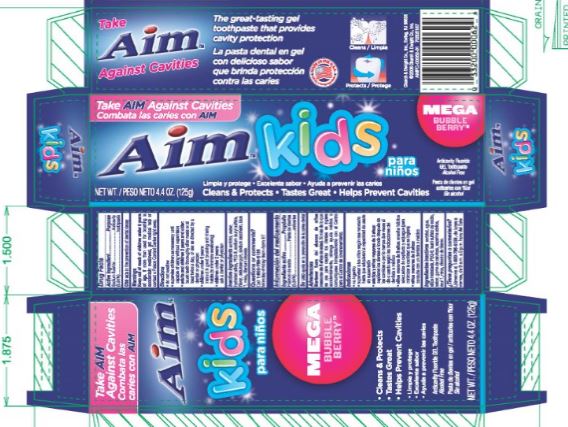 DRUG LABEL: AIM
NDC: 10237-625 | Form: GEL, DENTIFRICE
Manufacturer: Church & Dwight Co., Inc.
Category: otc | Type: HUMAN OTC DRUG LABEL
Date: 20241120

ACTIVE INGREDIENTS: SODIUM FLUORIDE 2.4 mg/1 g
INACTIVE INGREDIENTS: SORBITOL; WATER; HYDRATED SILICA; PEG-32 STEARATE; SODIUM LAURYL SULFATE; CARBOXYMETHYLCELLULOSE SODIUM; SACCHARIN SODIUM; FD&C BLUE NO. 1; MICA; TITANIUM DIOXIDE

AIM Bubble Berry

Active ingredients
Sodium fluoride (0.24%)

Purpose
Anticavity toothpaste

INDICATIONS AND USAGE

Use aids in the prevention of dental decay

Warnings
Keep out of reach of children under 6 years of age .

WARNINGS

If more than used for brushing is accidentally swallowed, get medical help or contact a Poison Control Center right away.

DOSAGE AND ADMINISTRATION

Directions do not swallow supervise children as necessary until capable of using without supervision

adults and children 2 years and older brush teeth thoroughly after meals or at least twice a day, or use as directed by a dentist or physician
children under 6 years instruct in good brushing and rinsing habits (to minimize swallowing)
children under 2 years ask a dentist or physician

INACTIVE INGREDIENT

Inactive ingredients sorbitol, water, hydrated silica, PEG-32, sodium lauryl sulfate, flavor, cellulose gum, sodium saccharin, blue 1, mica, titanium dioxide.

Questions or comments? Call 1-800-786-5135 Monday-Friday 9am-5pm ET

Principal Display Panel - AIM Kids

TAKE AIM AGAINST CAVITIES

AIM kids

MEGA Bubble Berry

NET WT. 4.4 OZ. (136g)

Cleans and Protects Tastes Great Helps Prevent Cavities
Anticavity Fluoride
Gel Toothpaste

Alcohol Free